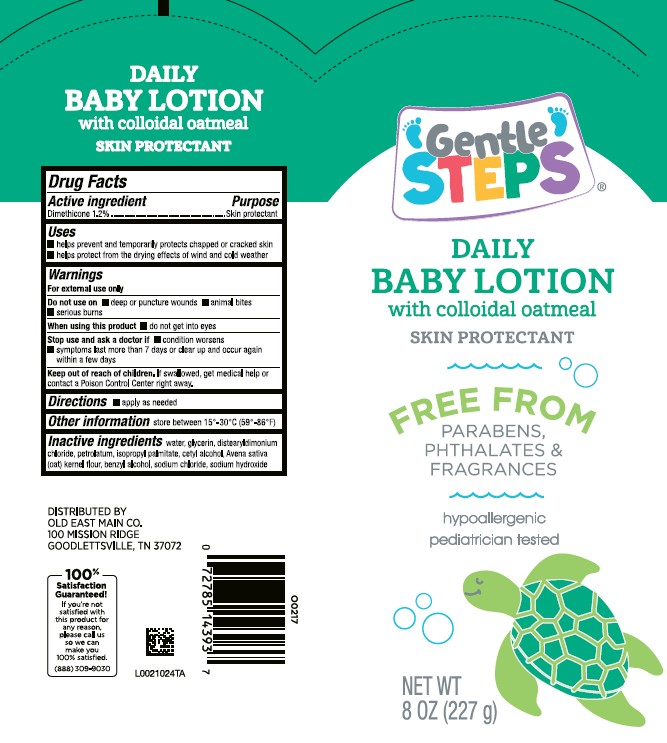 DRUG LABEL: Daily Moisturizing
NDC: 75712-496 | Form: LOTION
Manufacturer: Old East Main Co.
Category: otc | Type: HUMAN OTC DRUG LABEL
Date: 20260302

ACTIVE INGREDIENTS: DIMETHICONE 12 mg/1 g
INACTIVE INGREDIENTS: WATER; GLYCERIN; DISTEARYLDIMONIUM CHLORIDE; PETROLATUM; ISOPROPYL PALMITATE; CETYL ALCOHOL; OATMEAL; BENZYL ALCOHOL; SODIUM CHLORIDE; SODIUM HYDROXIDE

Gentle Steps 496.000/496AA
Daily Baby Lotion with Colloidal Oatmeal

Claims

DAILY BABY LOTION

with colloidal oatmeal

SKIN PROTECTANT

Active ingredient

Dimethicone 1.2%

Purpose

Skin protectant

Uses

- helps prevent and temporarily protects chapped or cracked skin
- helps protect from the drying effects of wind and cold weather

Warnings

For external use only

Do not use on

- deep or punture wounds
- animal bites
- serious burns

When using this product

do not get into eyes

Stop use and ask a doctor if

- condition worsens
- sympton last more than 7 days or clear up and occur again within a few days

Keep out of reach of children.

If swallowed, get medical help or contact a Poison Control Center right away.

Directions

- apply as needed

Other information

store between 15°-30°C (59°-86°F)

inactive ingredients

water, glycerin, distearyldimonium chloride, petrolatum, isopropyl palmitate, cetyl alcohol, Avena sativa (oat) kernel flour, benzyl alcohol, sodium chloride, sodium hydroxide

ADVERSE REACTION

DISTRIBUTED BY

OLD EAST MAIN CO.

100 MISSION RIDGE

GOODLETTSVILLE, TN 37072

100% Satisfaction Guaranteed! If you're not satisfied with this product for any reason, please call us so we can make you 100% satisfied.

(888)309-9030

principal panel display

Gentle Steps®

DAILY BABY LOTION

with colloidal oatmeal

SKIN PROTECTANT

Free From

Parabens, Phthalates & Fragrances

hypoallergenic

pediatrician tested

NET WT 8 Oz (227 g)